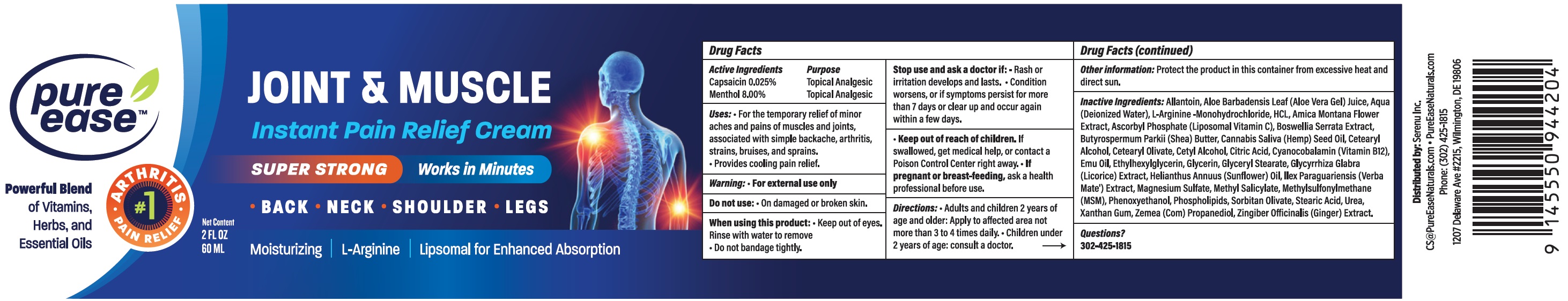 DRUG LABEL: PURE EASE Joint Muscle lnstant Pain Relief
NDC: 83676-435 | Form: CREAM
Manufacturer: SERENU, INC.
Category: otc | Type: HUMAN OTC DRUG LABEL
Date: 20231113

ACTIVE INGREDIENTS: CAPSAICIN 0.25 mg/1 mL; MENTHOL 80 mg/1 mL
INACTIVE INGREDIENTS: ALLANTOIN; ALOE VERA LEAF; WATER; ARGININE HYDROCHLORIDE; TALINEXOMER; ARNICA MONTANA FLOWER; MAGNESIUM ASCORBYL PHOSPHATE; INDIAN FRANKINCENSE; SHEA BUTTER; HEMP; CANNABIS SATIVA SEED OIL; CETOSTEARYL ALCOHOL; CETEARYL OLIVATE; CETYL ALCOHOL; CITRIC ACID MONOHYDRATE; CYANOCOBALAMIN; EMU OIL; ETHYLHEXYLGLYCERIN; GLYCERIN; GLYCERYL 1-STEARATE; GLYCYRRHIZA GLABRA; HELIANTHUS ANNUUS FLOWERING TOP; MAGNESIUM SULFATE, UNSPECIFIED FORM; METHYL SALICYLATE; DIMETHYL SULFONE; PHENOXYETHANOL; SORBITAN OLIVATE; STEARIC ACID; UREA; XANTHAN GUM; CORN; GINGER

PURE EASE Joint & Muscle lnstant pain Relief Cream

Active Ingredients

Capsaicin 0.025%

Menthol 8.00%

Purpose

Topical Analgesic

Uses:

- For the temporary relief of minor aches and pains of muscles and joints, associated with simple backache, arthritis, strains, bruises, and sprains.
- Provides cooling pain relief.

Warning:

For external use only

Do not use:

On damaged or broken skin.

When using this product:

Keep out of eyes. Rinse with water to remove

- Do not bandage tightly.

Stop use and ask a doctor if:

- Rash or irritation develops and lasts.
- Condition worsens, or if symptoms persist for more than 7 days or clear up and occur again within a few days.

Keep out of reach of children.

If swallowed, get medical help, or contact a Poison Control Center right away.

If pregnant or breast-feeding,

ask a health professional before use.

Directions:

Adults and children 2 years of age and older: Apply to affected area not more than 3 to 4 times daily. Children under 2 years of age: consult a doctor.

Other information:

Protect the product in this container from excessive heat and direct sun.

Inactive Ingredients:

Allantoin, Aloe Barbadnesis Leaf (Aloe Vera Gel) Juice, Aqua (Deionized Water), L-Arginine-Monohydrochloride, HCL, Amica Montana Flower Extract, Ascorbyl Phosphate (Liposomal Vitamin C), Boswellia Serrata Extract, Butyrospermum Parkii (Shea) Butter, Cannabis Saliva (Hemp) Seed Oil, Cetearyl Alcohol, Cetearyl Olivate, Cetyl Alcohol, Citric Acid, Cyanocobalamin (Vitamin B12), Emu Oil, Ethylhexylglycerin, Glycerin, Glyceryl Stearate, Glycyrrhiza Glabra (Licorice) Extract, Helianthus Annuus (Sunflower) Oil, Ilex Paraquariensis (Verba Mate') Extract, Magnesium Sulfate, Methylsulfonylmethane (MSM), Phenoxyethanol, Phospholipids, Sorbitan Olivate, Stearic Acid, Urea, Xanthan Gum, Zemea (Com) Propanediol, Zingiber Officinalis (Ginger) Extract.

Questions?

302-425-1815